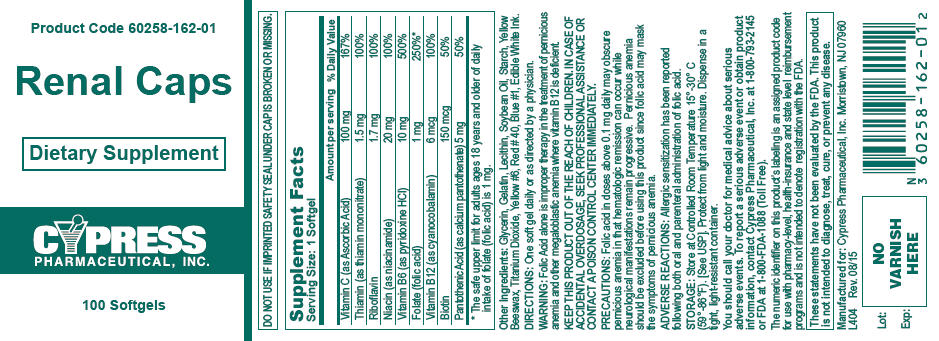 DRUG LABEL: Renal Caps
NDC: 60258-162 | Form: CAPSULE, LIQUID FILLED
Manufacturer: Cypress Pharmaceutical, Inc.
Category: prescription | Type: HUMAN PRESCRIPTION DRUG LABEL
Date: 20180104

ACTIVE INGREDIENTS: ASCORBIC ACID 100 mg/1 1; THIAMINE HYDROCHLORIDE 1.5 mg/1 1; RIBOFLAVIN 1.7 mg/1 1; NIACINAMIDE 20 mg/1 1; PYRIDOXINE HYDROCHLORIDE 10 mg/1 1; FOLIC ACID 1 mg/1 1; CYANOCOBALAMIN 6000 ug/1 1; BIOTIN 150000 ug/1 1; CALCIUM PANTOTHENATE 5 mg/1 1

Renal Caps

Description

Renal Caps are opaque black oval softgels imprinted "C 162". These softgels provide water-soluble vitamins. Renal Caps contain the following inactive ingredients: Blue 1 Lake, gelatin, glycerin, lecithin, Red 40 Lake, soybean oil, starch, titanium dioxide, Yellow # 6 Lake, yellow beeswax.

Each softgel contains:

Vitamin C (ascorbic acid)........................100 mg

Thiamine (as thiamine mononitrate)..........1.5 mg

Riboflavin...............................................1.7 mg

Niacin (as niacinamide).............................20 mg

Vitamin B6 (as pyridoxine HCl)...................10 mg

Folate (folic acid).........................................1mg

Vitamin B12 (as cyanocobalamin)...............6 mcg

Biotin....................................................150 mcg

Pantothenic Acid (as calcium pantothenate)..5 mg

Indications and Usage

Renal Caps is indicated in the wasting syndrome of chronic renal failure; uremia and impaired metabolic functions of the kidney. Renal Caps ia also highly effective as a stress vitamin.

Precautions

Folic acid may mask the symptoms of pernicious anemia in that hematologic remission may occur while neurological manifestations progress.

Dosage and Administration

One softgel daily, or as directed by physician. If on dialysis, take after treatment.

Storage

Store at controlled room temperature 15-30o C (59-86oF). Keep container tightly closed and protected from heat and moisture.

KEEP THIS AND ALL DRUGS OUT OF REACH OF CHILDREN.

Manufactured for Cypress Pharmaceutical, Inc.

Madison, MS 39110

L404 Rev 6/02

PRINCIPAL DISPLAY PANEL - 100 Softgel Bottle Label

Product Code 60258-162-01

Renal Caps

Dietary Supplement

CYPRESS
PHARMACEUTICAL, INC.

100 Softgels